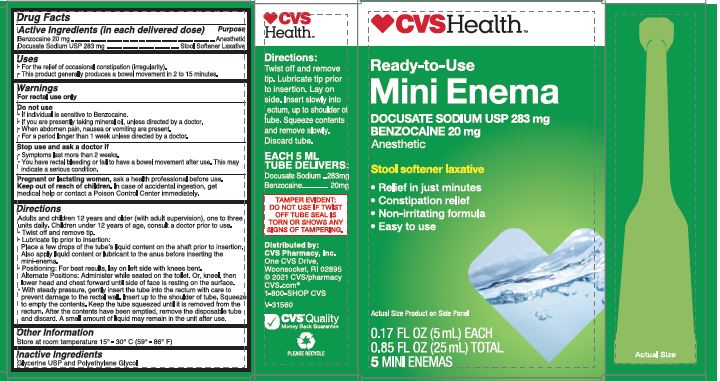 DRUG LABEL: CVS Mini Enema
NDC: 51316-991 | Form: LIQUID
Manufacturer: CVS HEALTH
Category: otc | Type: HUMAN OTC DRUG LABEL
Date: 20251204

ACTIVE INGREDIENTS: DOCUSATE SODIUM 283 mg/5 mL; BENZOCAINE 20 mg/5 mL
INACTIVE INGREDIENTS: POLYETHYLENE GLYCOL 300; GLYCERIN

CVSHealth Ready-to-Use Mini Enema

Drug Facts

Active Ingredients (per delivered dose)

Benzocaine 20 mg

Docusate Sodium USP 283 mg

Purpose

(Benzocaine).............. Anesthetic

(Docusate Sodium).... Stool Softener Laxative

Uses

- For the relief of occasional constipation (irregularity).
- This product generally produces a bowel movement in 2 to 15 minutes.

Warnings

For rectal use only.

Do not use

- If individual is sensitive to Benzocaine
- If you are presently taking mineral oil, unless directed by a doctor.
- When abdominal pain, nausea or vomiting are present.
- For a period longer than 1 week unless directed by a doctor.

Stop use and ask a doctor if:

- Symptoms last more than 2 weeks.
- You have rectal bleeding or fail to have a bowel movement after use. This may indicate a serious condition.

PREGNANCY OR BREAST FEEDING

Pregnant or Lactating Women, ask a health professional before use.

Keep out of reach of children. In case of accidental ingestion, get medical help or contact a Poison Control Center immediately.

Directions

Adults and children 12 years of age and older (with adult supervision) one to three units daily. Children under 12 years of age, consult a doctor prior to use.

- Twist off and remove tip.
- Lubricate tip prior to insertion: Place a few drops of the tube’s liquid content on the shaft prior to insertion. Also apply liquid content or lubricant to the anus before inserting the mini-enema.
- Positioning: For best results, lay on the left side with knees bent. Alternate Positions: Administer while seated on the toilet. Or, kneel, then lower head and chest forward until side of face is resting on the surface.
- With steady pressure, gently insert the tube into the rectum with care to prevent damage to the rectal wall. Insert up to the shoulder of tube. Squeeze to empty the contents. Keep the tube squeezed until it is removed from the rectum. After the contents have been emptied, remove the disposable tube and discard. A small amount of liquid may remain in the unit after use.

Other Information

Store at room temperature 15° - 30° C (59° - 86° F)

Inactive Ingredients

Glycerin USP and Polyethylene Glycol